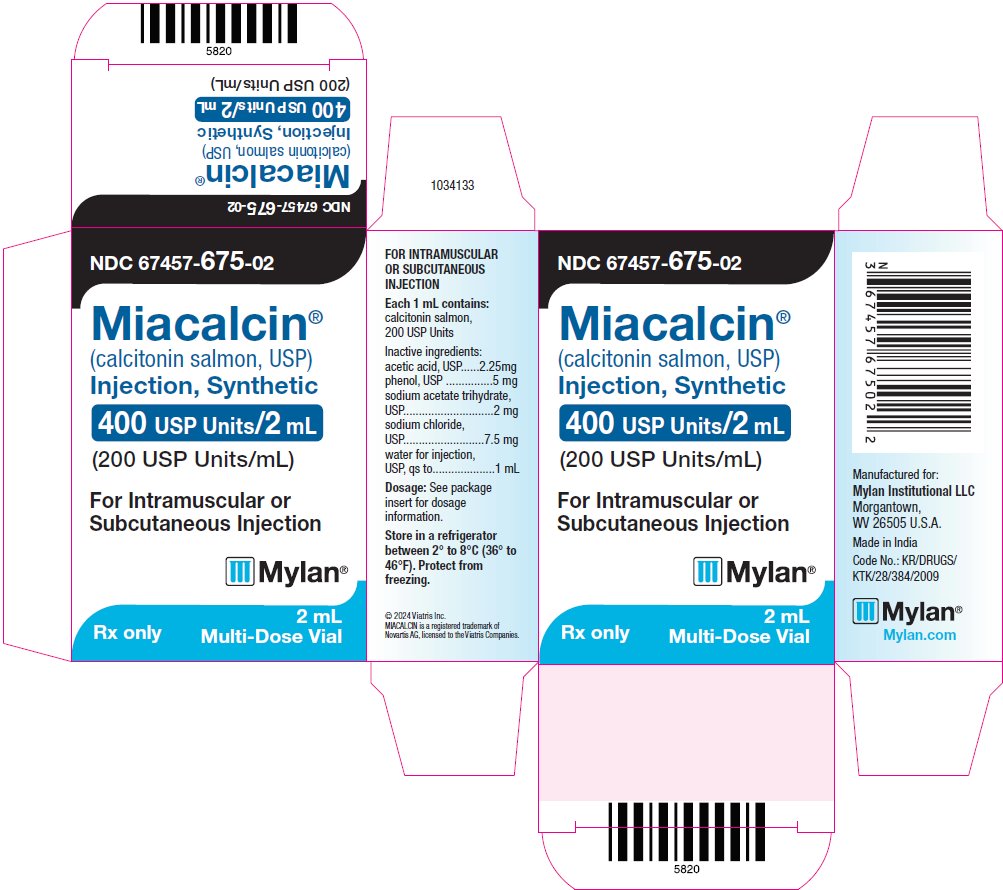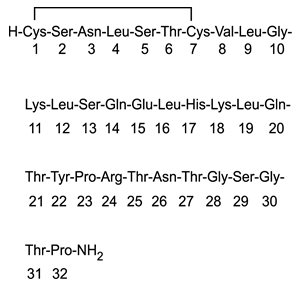 DRUG LABEL: Miacalcin
NDC: 67457-675 | Form: INJECTION, SOLUTION
Manufacturer: Mylan Institutional LLC
Category: prescription | Type: HUMAN PRESCRIPTION DRUG LABEL
Date: 20210815

ACTIVE INGREDIENTS: CALCITONIN SALMON 200 [USP'U]/1 mL
INACTIVE INGREDIENTS: ACETIC ACID 2.25 mg/1 mL; PHENOL 5 mg/1 mL; SODIUM ACETATE 2 mg/1 mL; SODIUM CHLORIDE 7.5 mg/1 mL; WATER

HIGHLIGHTS OF PRESCRIBING INFORMATION

These highlights do not include all the information needed to use MIACALCIN INJECTION safely and effectively. See full prescribing information for MIACALCIN INJECTION.
MIACALCIN® (calcitonin salmon) injection, synthetic, for subcutaneous or intramuscular use
Initial U.S. Approval: 1975

1 INDICATIONS AND USAGE

Miacalcin synthetic injection is a calcitonin, indicated for the following conditions:

- Treatment of symptomatic Paget’s disease of bone when alternative treatments are not suitable (1.1)
- Treatment of hypercalcemia (1.2)
- Treatment of postmenopausal osteoporosis when alternative treatments are not suitable. Fracture reduction efficacy has not been demonstrated (1.3)

Limitations of Use:

- Due to the possible association between malignancy and calcitonin salmon use, the need for continued therapy should be re-evaluated on a periodic basis (1.4, 5.3)

2 DOSAGE AND ADMINISTRATION

- Symptomatic Paget’s disease of bone: 100 USP Units daily. Ensure adequate calcium and vitamin D intake (2.1, 2.5)
- Hypercalcemia: start with 4 USP Units/kg body weight every 12 hours. Increase to 8 USP Units/kg every 12 hours if no improvement in 1-2 days. Increase further to 8 USP Units/kg every 6 hours if no improvement after 2 more days (2.2)
- Postmenopausal osteoporosis: 100 USP Units daily. Ensure adequate calcium and vitamin D intake (2.3, 2.5)

3 DOSAGE FORMS AND STRENGTHS

- Injection: 200 USP Units per mL sterile solution in 2 mL multi-dose vials (3)

4 CONTRAINDICATIONS

Hypersensitivity to calcitonin salmon or any of the excipients (4)

5 WARNINGS AND PRECAUTIONS

- Serious hypersensitivity reactions, including reports of fatal anaphylaxis have been reported. Consider skin testing prior to treatment in patients with suspected hypersensitivity to calcitonin salmon (5.1)
- Hypocalcemia has been reported. Ensure adequate intake of calcium and vitamin D (5.2)
- Malignancy: A meta-analysis of 21 clinical trials suggests an increased risk of overall malignancies in calcitonin salmon-treated patients (5.3, 6.1)
- Circulating antibodies to calcitonin salmon may develop, and may cause loss of response to treatment (5.4)

6 ADVERSE REACTIONS

Most common adverse reactions are nausea with or without vomiting (10%), injection site inflammation (10%), and flushing of the face or hands (2% to 5%) (6)

To report SUSPECTED ADVERSE REACTIONS, contact Mylan at 1-877-446-3679 (1-877-4-INFO-RX) or FDA at 1-800-FDA-1088 or www.fda.gov/medwatch.

7 DRUG INTERACTIONS

- Concomitant use of calcitonin salmon and lithium may lead to a reduction in plasma lithium concentrations due to increased urinary clearance of lithium. The dose of lithium may require adjustment (7)

8 USE IN SPECIFIC POPULATIONS

There are no data to support use in children (8.4)

FULL PRESCRIBING INFORMATION

1 INDICATIONS AND USAGE

1.1 Treatment of Paget’s Disease of Bone

Miacalcin injection is indicated for the treatment of symptomatic Paget’s disease of bone in patients with moderate to severe disease characterized by polyostotic involvement with elevated serum alkaline phosphatase and urinary hydroxyproline excretion. There is no evidence that the prophylactic use of calcitonin salmon is beneficial in asymptomatic patients. Miacalcin injection should be used only in patients who do not respond to alternative treatments or for whom such treatments are not suitable (e.g., patients for whom other therapies are contraindicated or for patients who are intolerant or unwilling to use other therapies).

1.2 Treatment of Hypercalcemia

Miacalcin injection is indicated for the early treatment of hypercalcemic emergencies, along with other appropriate agents, when a rapid decrease in serum calcium is required, until more specific treatment of the underlying disease can be accomplished. It may also be added to existing therapeutic regimens for hypercalcemia such as intravenous fluids and furosemide, oral phosphate or corticosteroids, or other agents.

1.3 Treatment of Postmenopausal Osteoporosis

Miacalcin injection is indicated for the treatment of postmenopausal osteoporosis in women greater than 5 years postmenopause. The evidence of efficacy for calcitonin salmon injection is based on increases in total body calcium observed in clinical trials. Fracture reduction efficacy has not been demonstrated. Miacalcin injection should be reserved for patients for whom alternative treatments are not suitable (e.g., patients for whom other therapies are contraindicated or for patients who are intolerant or unwilling to use other therapies).

1.4 Important Limitations of Use

Due to the possible association between malignancy and calcitonin salmon use, the need for continued therapy should be re-evaluated on a periodic basis [see Warnings and Precautions (5.3)].

2 DOSAGE AND ADMINISTRATION

2.1 Paget’s Disease of Bone

The recommended dose of Miacalcin injection for treatment of symptomatic Paget’s disease of bone is 100 USP Units (0.5 mL) per day administered subcutaneously or intramuscularly.

2.2 Hypercalcemia

The recommended starting dose of Miacalcin injection for early treatment of hypercalcemia is 4 USP Units/kg body weight every 12 hours by subcutaneous or intramuscular injection. If the response to this dose is not satisfactory after one or two days, the dose may be increased to 8 USP Units/kg every 12 hours. If the response remains unsatisfactory after two more days, the dose may be further increased to a maximum of 8 USP Units/kg every 6 hours.

2.3 Postmenopausal Osteoporosis

The recommended dose of Miacalcin injection for treatment of postmenopausal osteoporosis in women greater than 5 years postmenopause is 100 USP Units (0.5 mL) per day administered subcutaneously or intramuscularly. The minimum effective dose of Miacalcin injection for the prevention of vertebral bone mineral density loss has not been established.

2.4 Preparation and Administration

Visually inspect Miacalcin vials. Miacalcin injection is a clear, colorless, solution. If the solution is not clear and colorless, or contains any particles, or if the vial is damaged, do not administer the solution.

If the volume of Miacalcin injection to be injected exceeds 2 mL, intramuscular injection is preferable and the total dose should be distributed across multiple sites of injection.

Instruct patients to use sterile injection technique when administering Miacalcin injection, and to dispose of needles properly.

2.5 Recommendations for Calcium and Vitamin D Supplementation

Patients who use Miacalcin injection for treatment of postmenopausal osteoporosis should receive adequate calcium (at least 1000 mg elemental calcium per day) and vitamin D (at least 400 International Units per day).

3 DOSAGE FORMS AND STRENGTHS

Miacalcin injection is available as a clear, colorless, sterile solution of synthetic calcitonin salmon, USP in individual 2 mL multi-dose vials containing 200 USP Units per mL.

4 CONTRAINDICATIONS

Hypersensitivity to calcitonin salmon or any of the excipients. Reactions have included anaphylaxis with death, bronchospasm, and swelling of the tongue or throat [see Warnings and Precautions (5.1)].

5 WARNINGS AND PRECAUTIONS

5.1 Hypersensitivity Reactions

Serious hypersensitivity reactions have been reported in patients receiving Miacalcin injection, e.g., bronchospasm, swelling of the tongue or throat, anaphylactic shock, and death due to anaphylaxis. Appropriate medical support and monitoring measures should be readily available when Miacalcin injection is administered. If anaphylaxis or other severe hypersensitivity/allergic reactions occur, initiate appropriate treatment [see Contraindications (4)].

For patients with suspected hypersensitivity to calcitonin salmon, skin testing should be considered prior to treatment utilizing a dilute, sterile solution of Miacalcin injection. Healthcare providers may wish to refer patients who require skin testing to an allergist. A detailed skin testing protocol is available from the Mylan Pharmaceuticals Inc. Product Safety Department.

5.2 Hypocalcemia

Hypocalcemia associated with tetany (i.e., muscle cramps, twitching) and seizure activity has been reported with Miacalcin injection therapy. Hypocalcemia must be corrected before initiating therapy. Other disorders affecting mineral metabolism (such as vitamin D deficiency) should also be effectively treated. In patients at risk for hypocalcemia, provisions for parenteral calcium administration should be available during the first several administrations of calcitonin salmon and serum calcium and symptoms of hypocalcemia should be monitored. Use of Miacalcin injection for the treatment of Paget’s disease or postmenopausal osteoporosis is recommended in conjunction with an adequate intake of calcium and vitamin D [see Dosage and Administration (2.5)].

5.3 Malignancy

In a meta-analysis of 21 randomized, controlled clinical trials with calcitonin salmon (nasal spray or investigational oral formulations), the overall incidence of malignancies reported was higher among calcitonin salmon-treated patients (4.1%) compared with placebo-treated patients (2.9%). This suggests an increased risk of malignancies in calcitonin salmon-treated patients compared to placebo-treated patients. It is not possible to exclude an increased risk when calcitonin salmon is administered long-term subcutaneously, intramuscularly, or intravenously. The benefits for the individual patient should be carefully considered against possible risks [see Adverse Reactions (6.1)].

5.4 Antibody Formation

Circulating antibodies to calcitonin salmon have been reported with Miacalcin injection. The possibility of antibody formation should be considered in any patient with an initial response to Miacalcin injection who later stops responding to treatment [see Adverse Reactions (6.3)].

5.5 Urine Sediment Abnormalities

Coarse granular casts and casts containing renal tubular epithelial cells were reported in young adult volunteers at bed rest who were given injectable calcitonin salmon to study the effect of immobilization on osteoporosis. There was no other evidence of renal abnormality and the urine sediment normalized after calcitonin salmon was stopped. Periodic examinations of urine sediment should be considered.

6 ADVERSE REACTIONS

The following serious adverse reactions are discussed in greater detail in other sections of the label:

- Hypersensitivity Reactions, including anaphylaxis [see Warnings and Precautions (5.1)]
- Hypocalcemia [see Warnings and Precautions (5.2)]
- Malignancy [see Warnings and Precautions (5.3)]

6.1 Clinical Trials Experience

Because clinical trials are conducted under widely varying conditions, adverse reaction rates observed in the clinical trials of a drug cannot be directly compared to rates in the clinical trials of another drug and may not reflect the rates observed in practice.

The safety of calcitonin salmon injection was assessed in open-label trials several months to two years in duration. The most common adverse reactions are discussed below.

Nausea

Nausea with or without vomiting has been noted in about 10% of patients treated with calcitonin salmon. It is most evident when treatment is first initiated and tends to decrease or disappear with continued administration.

Dermatologic Reactions

Local inflammatory reactions at the site of subcutaneous or intramuscular injection have been reported in about 10% of patients. Flushing of face or hands occurred in about 2% to 5% of patients. Skin rashes and pruritus of the ear lobes have also been reported.

Other Adverse Reactions

Nocturia, feverish sensation, pain in the eyes, poor appetite, abdominal pain, pedal edema, and salty taste have been reported in patients treated with calcitonin salmon injection.

Malignancy

A meta-analysis of 21 randomized, controlled clinical trials with calcitonin salmon (nasal spray or investigational oral formulations) was conducted to assess the risk of malignancies in calcitonin salmon-treated patients compared to placebo-treated patients. The trials in the meta-analysis ranged in duration from 6 months to 5 years and included a total of 10883 patients (6151 treated with calcitonin salmon and 4732 treated with placebo). The overall incidence of malignancies reported in these 21 trials was higher among calcitonin salmon-treated patients (254/6151 or 4.1%) compared with placebo-treated patients (137/4732 or 2.9%). Findings were similar when analyses were restricted to the 18 nasal spray only trials [calcitonin salmon 122/2712 (4.5%); placebo 30/1309 (2.3%)].

The meta-analysis results suggest an increased risk of overall malignancies in calcitonin salmon-treated patients compared to placebo-treated patients when all 21 trials are included and when the analysis is restricted to the 18 nasal spray only trials (see Table 1). It is not possible to exclude an increased risk when calcitonin salmon is administered by the subcutaneous, intramuscular, or intravenous route because these routes of administration were not investigated in the meta-analysis. The increased malignancy risk seen with the meta-analysis was heavily influenced by a single large 5-year trial, which had an observed risk difference of 3.4% [95% CI (0.4%, 6.5%)]. Imbalances in risks were still observed when analyses excluded basal cell carcinoma (see Table 1); the data were not sufficient for further analyses by type of malignancy. A mechanism for these observations has not been identified. Although a definitive causal relationship between calcitonin salmon use and malignancies cannot be established from this meta-analysis, the benefits for the individual patient should be carefully evaluated against all possible risks [see Warnings and Precautions (5.3)].

Table 1: Risk Difference for Malignancies in Calcitonin Salmon-Treated Patients Compared with Placebo-Treated Patients
Patients | Malignancies | Risk Difference [The overall adjusted risk difference is the difference between the percentage of patients who had any malignancy (or malignancy excluding basal cell carcinoma) in calcitonin salmon and placebo treatment groups, using the Mantel-Haenszel (MH) fixed-effect method. A risk difference of 0 is suggestive of no difference in malignancy risks between the treatment groups.] (%) | 95% Confidence Interval [The corresponding 95% confidence interval for the overall adjusted risk difference also based on MH fixed-effect method.] (%)
All (nasal spray + oral) | All | 1.0 | (0.3, 1.6)
All (nasal spray + oral) | Excluding basal cell carcinoma | 0.5 | (-0.1, 1.2)
All (nasal spray only) | All | 1.4 | (0.3, 2.6)
All (nasal spray only) | Excluding basal cell carcinoma | 0.8 | (-0.2, 1.8)

6.2 Postmarketing Experience

Because postmarketing adverse reactions are reported voluntarily from a population of uncertain size, it is not always possible to reliably estimate their frequency or establish a causal relationship to drug exposure.

The following adverse reactions have been reported during post-approval use of Miacalcin injection.

Allergic / Hypersensitivity Reactions: Serious hypersensitivity reactions have been reported in patients receiving calcitonin salmon injection, e.g., bronchospasm, swelling of the tongue or throat, anaphylactic shock, and death due to anaphylaxis.

Skin and subcutaneous tissue disorders: Urticaria

Hypocalcemia: Hypocalcemia with tetany (i.e. muscle cramps, twitching) and seizure activity have been reported.

Body as a Whole: influenza-like symptoms, fatigue, edema (facial, peripheral, and generalized)

Musculoskeletal: arthralgia, musculoskeletal pain

Cardiovascular: hypertension

Gastrointestinal: abdominal pain, diarrhea

Urinary System: polyuria

Nervous System: dizziness, headache, paresthesia, tremor

Vision: visual disturbance

6.3 Immunogenicity

Consistent with the potentially immunogenic properties of medicinal products containing peptides, administration of Miacalcin may trigger the development of anti-calcitonin antibodies. Circulating antibodies to calcitonin salmon after 2 to 18 months of treatment have been reported in about one-half of the patients with Paget’s disease in whom antibody studies were done. In some cases, high antibody titers are found; these patients usually will have a loss of response to treatment [see Warnings and Precautions (5.4)].

The incidence of antibody formation is highly dependent on the sensitivity and specificity of the assay. Additionally, the observed incidence of a positive antibody test result may be influenced by several factors, including assay methodology, sample handling, timing of sample collection, concomitant medications, and underlying disease. For these reasons, comparison of antibodies among different calcitonin salmon products may be misleading.

7 DRUG INTERACTIONS

No formal drug interaction studies have been performed with Miacalcin injection.

Concomitant use of calcitonin salmon and lithium may lead to a reduction in plasma lithium concentrations due to increased urinary clearance of lithium. The dose of lithium may require adjustment.

8 USE IN SPECIFIC POPULATIONS

8.1 Pregnancy

Risk Summary

There are no studies with Miacalcin injection in pregnant women to inform a drug associated risk for birth defects or miscarriage. In an animal reproduction study, subcutaneous administration of calcitonin salmon to pregnant rabbits during organogenesis at 4-18 times the recommended parenteral human dose caused a decrease in fetal birth weights. No adverse developmental outcome was observed in the rat with subcutaneous administration of calcitonin salmon at 9 times the recommended human parenteral dose based on body surface area (see Data).

In the U.S. general population, the estimated background risk of major birth defects and miscarriage in clinically recognized pregnancies is 2-4% and 15-20%, respectively.

Data

Animal Data

Calcitonin salmon has been shown to cause a decrease in fetal birth weights in rabbits when given by subcutaneous injection in doses 4 to 18 times the parenteral dose recommended for human use (of 54 International Units/m^2).

No embryo/fetal toxicities related to Miacalcin were reported from maternal subcutaneous daily doses in rats up to 80 International Units/kg/day from gestation day 6 to 15.

8.2 Lactation

Risk Summary

There is no information on the presence of calcitonin salmon in human milk, the effects on the breastfed child, or the effects on milk production. Calcitonin has been shown to inhibit lactation in rats. The developmental and health benefits of breastfeeding should be considered along with the mother’s clinical need for Miacalcin injection and any potential adverse effects on the breastfed infant from Miacalcin injection or from the underlying maternal condition.

8.4 Pediatric Use

Safety and effectiveness in pediatric patients have not been established.

8.5 Geriatric Use

Clinical studies of Miacalcin injection did not include sufficient numbers of subjects aged 65 years and older to determine whether they respond differently from younger subjects. Other reported clinical experience has not identified differences in responses between the elderly and younger patients. In general, dose selection for an elderly patient should be cautious, usually starting at the low end of the dosing range, reflecting the greater frequency of decreased hepatic, renal, or cardiac function, and of concomitant disease or other drug therapy.

10 OVERDOSAGE

The pharmacologic actions of Miacalcin injection suggest that hypocalcemic tetany could occur in overdose. Therefore, provisions for parenteral administration of calcium should be available for the treatment of overdose.

A dose of calcitonin salmon l000 International Units subcutaneously may produce nausea and vomiting. Doses of 32 International Units per kg per day for 1 to 2 days demonstrate no other adverse effects. Data on chronic high-dose administration are insufficient to assess toxicity.

11 DESCRIPTION

Calcitonin is a polypeptide hormone secreted by the parafollicular cells of the thyroid gland in mammals and by the ultimobranchial gland of birds and fish.

Miacalcin (calcitonin salmon, USP) Injection, Synthetic is a synthetic polypeptide of 32 amino acids in the same linear sequence that is found in calcitonin of salmon origin. This is shown by the following graphic formula:

It is provided in sterile solution for subcutaneous or intramuscular injection. Each milliliter contains: calcitonin salmon, 200 USP Units.

Inactive Ingredients (per mL): acetic acid, USP, 2.25 mg; phenol, USP, 5 mg; sodium acetate trihydrate, USP, 2 mg; sodium chloride, USP, 7.5 mg; water for injection, USP.

The activity of Miacalcin injection is stated in International Units based on bioassay in comparison with the International Reference Preparation of calcitonin salmon for Bioassay, distributed by the National Institute for Biological Standards and Control, Holly Hill, London.

12 CLINICAL PHARMACOLOGY

12.1 Mechanism of Action

Calcitonin salmon is a calcitonin receptor agonist. Calcitonin salmon acts primarily on bone, but direct renal effects and actions on the gastrointestinal tract are also recognized. Calcitonin salmon appears to have actions essentially identical to calcitonins of mammalian origin, but its potency per mg is greater and it has a longer duration of action.

The actions of calcitonin on bone and its role in normal human bone physiology are still not completely elucidated, although calcitonin receptors have been discovered in osteoclasts and osteoblasts.

12.2 Pharmacodynamics

Bone

Single injections of calcitonin salmon caused a marked transient inhibition of the ongoing bone resorptive process. With prolonged use, there is a persistent, smaller decrease in the rate of bone resorption. Histologically, this is associated with a decreased number of osteoclasts and an apparent decrease in their resorptive activity.

In healthy adults, who have a relatively low rate of bone resorption, the administration of exogenous calcitonin salmon results in decreases in serum calcium within the limits of the normal range. In healthy children and in patients whose bone resorption is more rapid, decreases in serum calcium are more pronounced in response to calcitonin salmon.

Kidney

Studies with injectable calcitonin salmon show increases in the excretion of filtered phosphate, calcium, and sodium by decreasing their tubular reabsorption.

Gastrointestinal Tract

Some evidence from studies with injectable preparations suggests that calcitonin salmon may have effects on the gastrointestinal tract. Short-term administration of injectable calcitonin salmon results in marked transient decreases in the volume and acidity of gastric juice and in the volume and the trypsin and amylase content of pancreatic juice. Whether these effects continue to be elicited after each injection of calcitonin salmon during chronic therapy has not been investigated.

12.3 Pharmacokinetics

The absolute bioavailability of calcitonin salmon is approximately 66% and 71% after intramuscular or subcutaneous injection, respectively. After subcutaneous administration, peak plasma levels are reached in approximately 23 minutes. The terminal half-life is approximately 58 minutes for intramuscular administration and 59 to 64 minutes for subcutaneous administration. The apparent volume of distribution is 0.15 to 0.3 L/kg.

13 NONCLINICAL TOXICOLOGY

13.1 Carcinogenesis, Mutagenesis, Impairment of Fertility

Carcinogenicity

The incidence of pituitary adenomas was increased in rats after one and two years of subcutaneous exposure to synthetic calcitonin salmon. The significance of this finding to humans is unknown because pituitary adenomas are very common in rats as they age, the pituitary adenomas did not transform into metastatic tumors, there were no other clear treatment-related neoplasms, and synthetic calcitonin salmon related neoplasms were not observed in mice after two years of dosing.

Rat findings

The only clear neoplastic finding in rats dosed subcutaneously with calcitonin salmon was an increase in the incidence of pituitary adenomas in male Fisher 344 rats and female Sprague Dawley rats after one year of dosing and male Sprague Dawley rats dosed for one and two years. In female Sprague Dawley rats, the incidence of pituitary adenomas after two years was high in all treatment groups (between 80% and 92% including the control groups) such that a treatment-related effect could not be distinguished from natural background incidence. The lowest dose in male Sprague Dawley rats that developed an increased incidence of pituitary adenomas after two years of dosing (1.7 International Units/kg/day) is approximately 1/6th of the maximum recommended subcutaneous dose in humans (100 International Units/day) based on body surface area conversion between rats and humans. The findings suggest that calcitonin salmon reduced the latency period for development of non-functioning pituitary adenomas.

Mouse findings

No carcinogenicity potential was evident in male or female mice dosed subcutaneously for two years with synthetic calcitonin salmon at doses up to 800 International Units/kg/day. The 800 International Units/kg/day dose is approximately 39 times the maximum recommended subcutaneous dose in humans (100 International Units/day) based on body surface area conversion between mice and humans.

Mutagenesis

Synthetic calcitonin salmon tested negative for mutagenicity using Salmonella typhimurium (5 strains) and Escherichia coli (2 strains), with and without rat liver metabolic activation, and was not clastogenic in a chromosome aberration test in Chinese Hamster V79 cells. There was no evidence that calcitonin salmon was clastogenic in the in vivo mouse micronucleus test.

Fertility

Effects of calcitonin salmon on fertility have not been assessed in animals.

14 CLINICAL STUDIES

14.1 Paget’s Disease of Bone

The trials used for the basis of approval for calcitonin salmon injection for treatment of Paget’s disease of bone were conducted in patients with moderate to severe disease characterized by polyostotic involvement with elevated serum alkaline phosphatase and urinary hydroxyproline excretion. In open-label clinical trials of several months to two years duration with historical controls, biochemical abnormalities were substantially improved (more than 30% reduction) in about 2/3 of patients studied and bone pain was improved in a similar fraction. A small number of documented instances of reversal of neurologic deficits have occurred, including improvement in the basilar compression syndrome, and improvement of spinal cord and spinal nerve lesions. There is too little experience to predict the likelihood of improvement of any given neurologic lesion. Hearing loss is improved infrequently (4 of 29 patients studied by audiometry). Patients with increased cardiac output due to extensive Paget’s disease of bone have had measured decreases in cardiac output while receiving calcitonin salmon. The number of treated patients in this category is too small to predict how likely such a result will be.

There is no evidence that the prophylactic use of calcitonin salmon is beneficial in asymptomatic patients.

14.2 Hypercalcemia

In four open-label clinical trials enrolling 53 patients, calcitonin salmon has been shown to lower elevated serum calcium levels of patients with carcinoma (with or without metastases), multiple myeloma, and primary hyperparathyroidism (lesser response). These patients were treated with calcitonin salmon only when other methods of lowering serum calcium (hydration, oral phosphate, corticosteroids) were unsuccessful or unsuitable. With patients’ pre-therapy serum calcium levels as controls, reduction in serum calcium was evident within 1 to 2 hours of administration. The peak effect occurred within 24 to 48 hours of injection and administration of calcitonin salmon every 12 hours maintained a hypocalcemic effect for approximately 5 to 8 days, the time period evaluated for most patients in the clinical trials. The average reduction of 8-hour post-injection serum calcium was approximately 9% (2 to 3 mg/dL). Patients with higher values of serum calcium tended to show greater reductions during calcitonin salmon treatment.

14.3 Postmenopausal Osteoporosis

The trials used for the basis of approval for calcitonin salmon injection for treatment of postmenopausal osteoporosis were two randomized, open-label, 2-year studies in postmenopausal women 50 to 74 years of age with total body calcium < 85% of expected normal, and vertebral osteopenia (by x-ray criteria) and/or at least one atraumatic compression fracture. The primary efficacy endpoint was total body calcium measured by neutron activation analysis. Patients were randomized to calcitonin salmon injection 100 International Units daily (subcutaneously or intramuscularly) at bedtime, or control. All subjects received daily supplements of 1200 mg calcium carbonate and 400 International Units of vitamin D.

In both studies, total body calcium increased from baseline with calcitonin salmon therapy at 1 year, followed by a trend to decreasing total body calcium (still above baseline) at 2 years.

Thoracic and lumbar spine X-rays (AP/lateral) were obtained yearly. For the two studies combined (34 calcitonin salmon and 35 control subjects), in the first year there was a total of 6 new vertebral compression fractures in the calcitonin salmon group and 5 in the control group. In the second year there were 7 new fractures in each group.

No evidence currently exists to indicate whether Miacalcin injection decreases the risk of osteoporotic fracture. A controlled study, which was prematurely discontinued, failed to demonstrate any benefit of calcitonin salmon on fracture rate.

No adequate controlled trials have examined the effect of calcitonin salmon injection on vertebral bone mineral density beyond 1 year of treatment. Therefore, the minimum effective dose of Miacalcin injection for prevention of vertebral bone mineral density loss has not been established.

In clinical studies of postmenopausal osteoporosis, bone biopsy and radial bone mass assessments at baseline and after 26 months of daily injectable calcitonin salmon indicate that calcitonin therapy results in the formation of normal bone.

16 HOW SUPPLIED/STORAGE AND HANDLING

How Supplied

Miacalcin (calcitonin salmon, USP) Injection, Synthetic is available as a sterile solution in individual 2 mL multi-dose vials containing 200 USP Units per mL.

NDC 67457-675-02
carton containing 1 x 2 mL multi-dose vial

Storage and Handling

Store in a refrigerator between 2° to 8°C (36° to 46°F).

Protect from freezing.

17 PATIENT COUNSELING INFORMATION

- Instruct patients and other persons who may administer Miacalcin injection in sterile injection technique. Also instruct patients to dispose of needles properly [see Dosage and Administration (2.4)].
- Inform patients of the potential increase in risk of malignancy [see Warnings and Precautions (5.3)].
- Advise patients with postmenopausal osteoporosis or Paget’s disease of bone to maintain an adequate calcium (at least 1000 mg elemental calcium per day) and vitamin D (at least 400 International Units per day) intake [see Dosage and Administration (2.5)].
- Instruct patients to seek emergency medical help or go to the nearest hospital emergency room right away if they develop any signs or symptoms of a serious allergic reaction [see Warnings and Precautions (5.1)].

Manufactured for:
Mylan Institutional LLC
Morgantown, WV 26505 U.S.A.

Manufactured by:
Alcami Corporation
Charleston, SC 29405 U.S.A.

MI:MIACIJ:R5
PC4898D

© 2021 Viatris Inc.

MIACALCIN is a registered trademark of Novartis AG, licensed to the Viatris Companies.

PRINCIPAL DISPLAY PANEL – 400 USP Units/2 mL

NDC 67457-675-02

Miacalcin®
(calcitonin salmon, USP)
Injection, Synthetic
400 USP Units/2 mL
(200 USP Units/mL)

For Intramuscular or
Subcutaneous Injection

Rx only 2 mL Multi-Dose Vial

FOR INTRAMUSCULAR
OR SUBCUTANEOUS
INJECTION

Each 1 mL contains:
calcitonin salmon,
200 USP Units

Inactive ingredients:
acetic acid, USP......2.25mg
phenol, USP ...............5 mg
sodium acetate trihydrate,
USP.............................2 mg
sodium chloride,
USP..........................7.5 mg
water for injection,
USP, qs to....................1 mL

Dosage: See package
insert for dosage
information.

Store in a refrigerator
between 2° to 8°C (36° to
46°F). Protect from
freezing.

© 2024 Viatris Inc
MIACALCIN is a registered trademark of
Novartis AG, licensed to the Viatris Companies

Manufactured for:
Mylan Institutional LLC
Morgantown,
WV 26505 U.S.A.

Made in India

Code No.: KR/DRUGS/
KTK/28/384/2009

Mylan.com